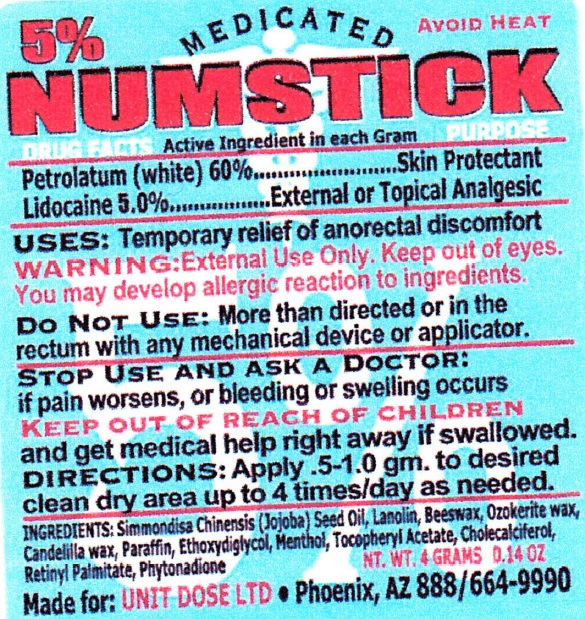 DRUG LABEL: Numstick
NDC: 67194-014 | Form: STICK
Manufacturer: Unit Dose, Ltd.
Category: otc | Type: HUMAN OTC DRUG LABEL
Date: 20231018

ACTIVE INGREDIENTS: PETROLATUM 600 mg/1 g; LIDOCAINE 50 mg/1 g
INACTIVE INGREDIENTS: JOJOBA OIL; LANOLIN; YELLOW WAX; CERESIN; CANDELILLA WAX; PARAFFIN; DIETHYLENE GLYCOL MONOETHYL ETHER; MENTHOL; .ALPHA.-TOCOPHEROL ACETATE; CHOLECALCIFEROL; VITAMIN A PALMITATE; PHYTONADIONE

Numstick

Active Ingredient in each Gram

Petrolatum (White) 60%

Lidocaine 5.0%

PURPOSE

Skin Protectant

External or Topical Analgesic

USES:

Temporary relief of anorectal discomfort

WARNING:

External Use Only. Keep out of eyes.. You may develop allergic reaction to ingredients.

Do Not Use:

More than directed or in the rectum with any mechanical device or applicator.

STOP USE AND ASK A DOCTOR:

if pain worsens, or bleeding or swelling occurs

KEEP OUT OF REACH OF CHILDREN

and get medical help right away if swallowed.

DIRECTIONS:

Apply .5-1.0 gm. to desired clean dry area up to 4 times/day as needed.

INGREDIENTS:

Simmondisa Chinensis (Jojoba) Seed oil, Lanolin, Beeswax, Ozokerite wax, Candelilla wax, Paraffin, Ethoxydiglycol, Menthol, Tocopheryl Acetate, Cholecalciferol, Retinyl Palmitate, Phytonadione